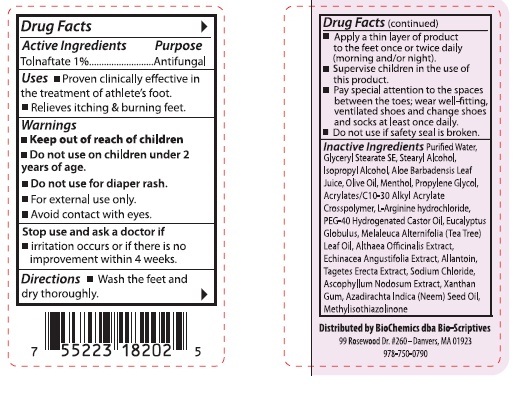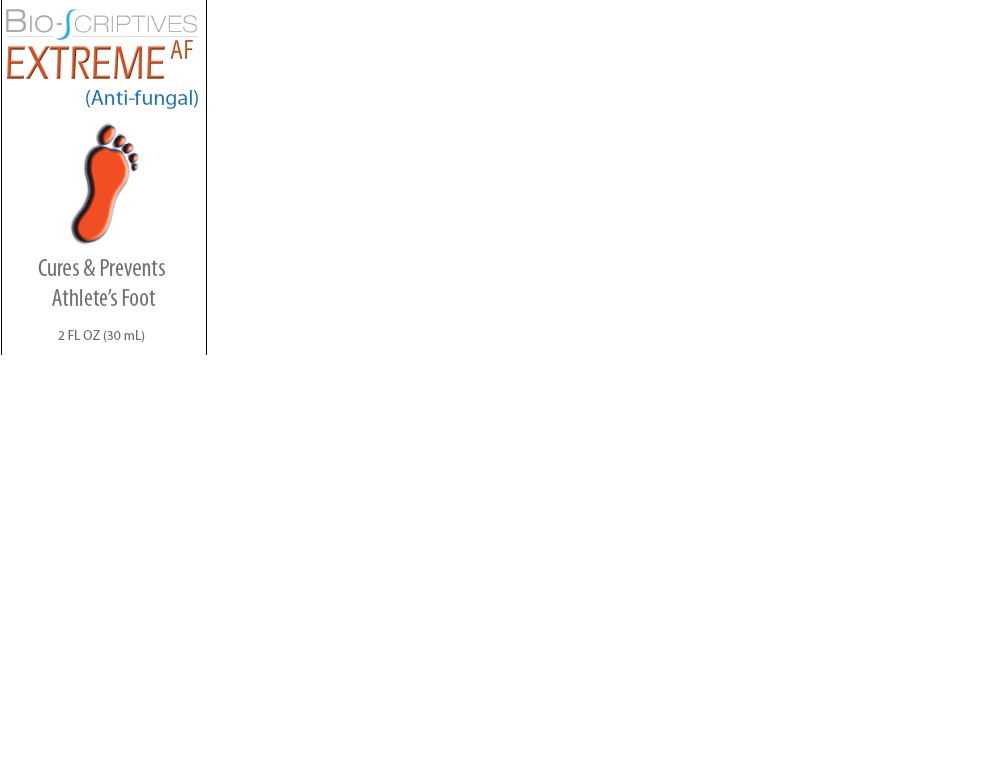 DRUG LABEL: Bio-Scriptives Extreme AF
NDC: 60608-013 | Form: CREAM
Manufacturer: BioChemics, Inc.
Category: otc | Type: HUMAN OTC DRUG LABEL
Date: 20110727

ACTIVE INGREDIENTS: TOLNAFTATE .56 g/56.69 g
INACTIVE INGREDIENTS: CARBOMER COPOLYMER TYPE A; PROPYLENE GLYCOL; XANTHAN GUM; WATER; ARGININE HYDROCHLORIDE; SODIUM CHLORIDE; ALOE VERA LEAF; ALLANTOIN; ALTHAEA OFFICINALIS ROOT; ECHINACEA ANGUSTIFOLIA LEAF; ASCOPHYLLUM NODOSUM; TAGETES ERECTA FLOWER; STEARYL ALCOHOL; METHYLISOTHIAZOLINONE; MENTHOL; EUCALYPTUS GLOBULUS LEAF; GLYCERYL MONOSTEARATE; OLIVE OIL; POLYOXYL 40 HYDROGENATED CASTOR OIL; AZADIRACHTA INDICA SEED OIL; ISOPROPYL ALCOHOL; MELALEUCA ALTERNIFOLIA LEAF

Drug Facts

Active Ingredients

Tolnaftate 1%

Purpose

Antifungal

Uses

■ Proven clinically effective in the treatment of athlete's foot.
■ Relieves itching and burning feet.

Warnings

■ Do not use on children under 2 years of age.
■ Do not use for diaper rash.
■ For external use only.
■ Avoid contact with eyes.

Stop use and ask a doctor if

- irritation occurs or if there is no improvement within 4 weeks.

Directions

■ Wash the feet and dry thoroughly.
■ Apply a thin layer of product to the feet once or twice daily (morning and/or night).
■ Supervise children in the use of this product.
■ Pay special attention to the spaces between the toes; wear well-fitting, ventilated shoes and change shoes and socks at least once daily.
■ Do not use if safety seal is broken.

Inactive Ingredients

Purified Water, Glyceryl Stearate SE, Stearyl Alcohol, Isopropyl Alcohol, Aloe Barbadensis Leaf Juice, Olive Oil, Menthol, Propylene Glycol, Acrylates/C10-30 Alkyl Acrylate Crosspolymer, L-Arginine hydroxide, PEG-40 Hdrogenated Castor Oil, Eucalyptus Globulus, Melaleuca Alternifolia (Tea Tree) Leaf Oil, Althaea Officinalis Extract, Echinacea Angustifolia Extract, Allantoin, Tagetes Erecta Extract, Sodium Chloride, Ascophyllum Nodosum Extract, Xanthan Gum, Azadirachta Indica (Neem) Seed Oil, Methylisothiazolinone

Reference

Distributed by BioChemics dba Bio-Scriptives

99 Rosewood Dr. #260 - Danvers, MA 01923

978-750-0790

Keep out of reach of children

Enter section text here